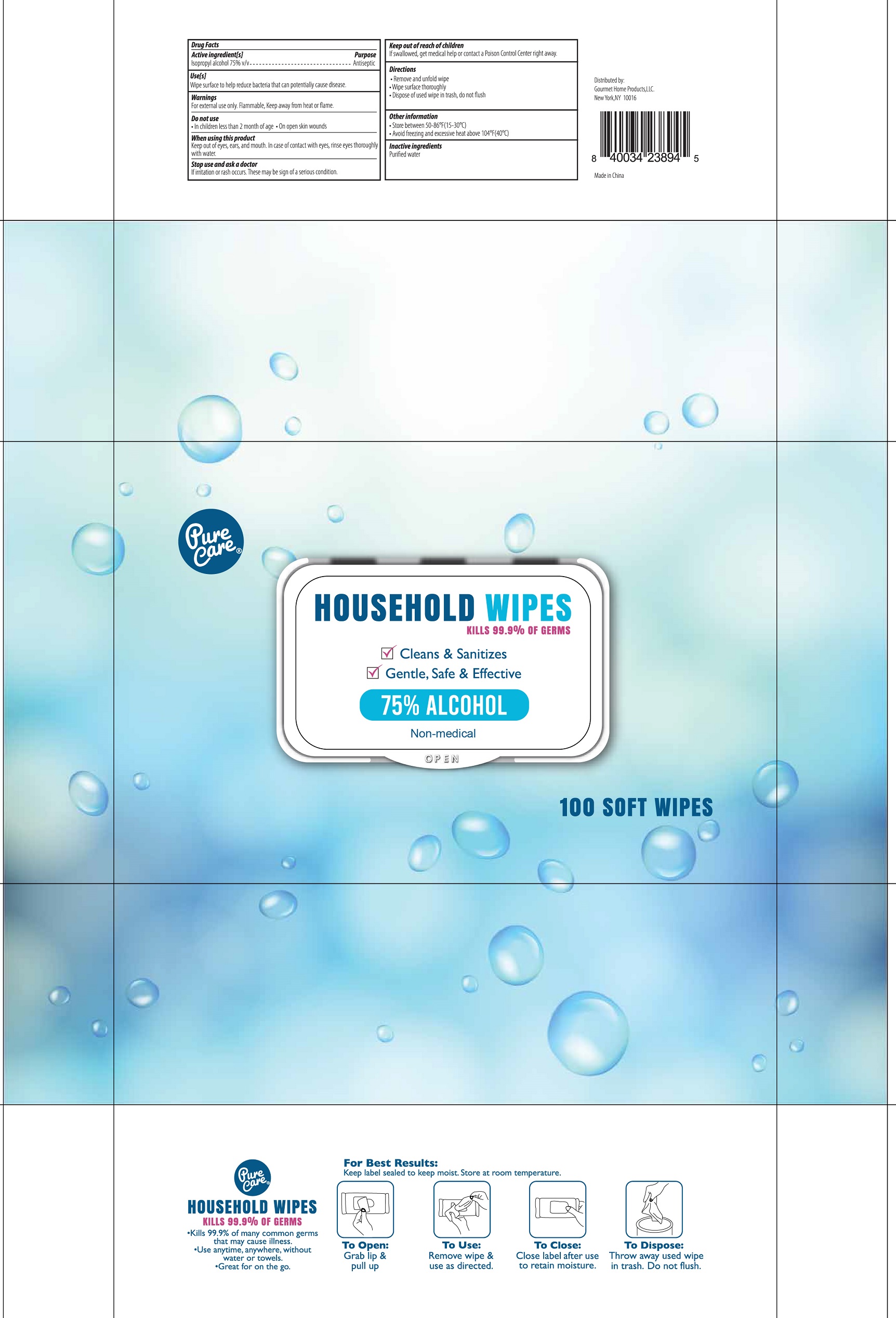 DRUG LABEL: Pure Care Alcohol Wipes
NDC: 77909-008 | Form: CLOTH
Manufacturer: Zhejiang Huihao Daily Products Co.,Ltd
Category: otc | Type: HUMAN OTC DRUG LABEL
Date: 20200826

ACTIVE INGREDIENTS: ALCOHOL 75 g/100 g
INACTIVE INGREDIENTS: water

Wipes

Active Ingredient

Isopropyl Alcohol 75% v/v

Purpose

Antiseptic

USES

Wipes surface to help reduce bacteria that can potentially cause disease.

Warnings

- For external use only.
- Flammable, Keep away from heat or flame

Do not use

In children less than 2 month of age

On open skin wounds.

When using this product

keep out of eyes, ears, and mouth. In case of contact with eyes, rinse eyes thoroughly with water.

Stop use and ask a doctor If

If irritation or rash occurs. These may be sign of a serious condition.

KEEP OUT OF REACH OF CHILDREN

If swallowed, get medical help or contact a Poison Contrl Center right away.

Directions

- Remove and unfold wipe
- Wipe surface thoroughly
- Dispose of used wipe in trash, do not flush

Other information:

- Store between 50-86 ℉ (15-30℃)
- Avoid freezing and excessive heat above 104℉ (40℃)

Inactive ingredients

Purified water